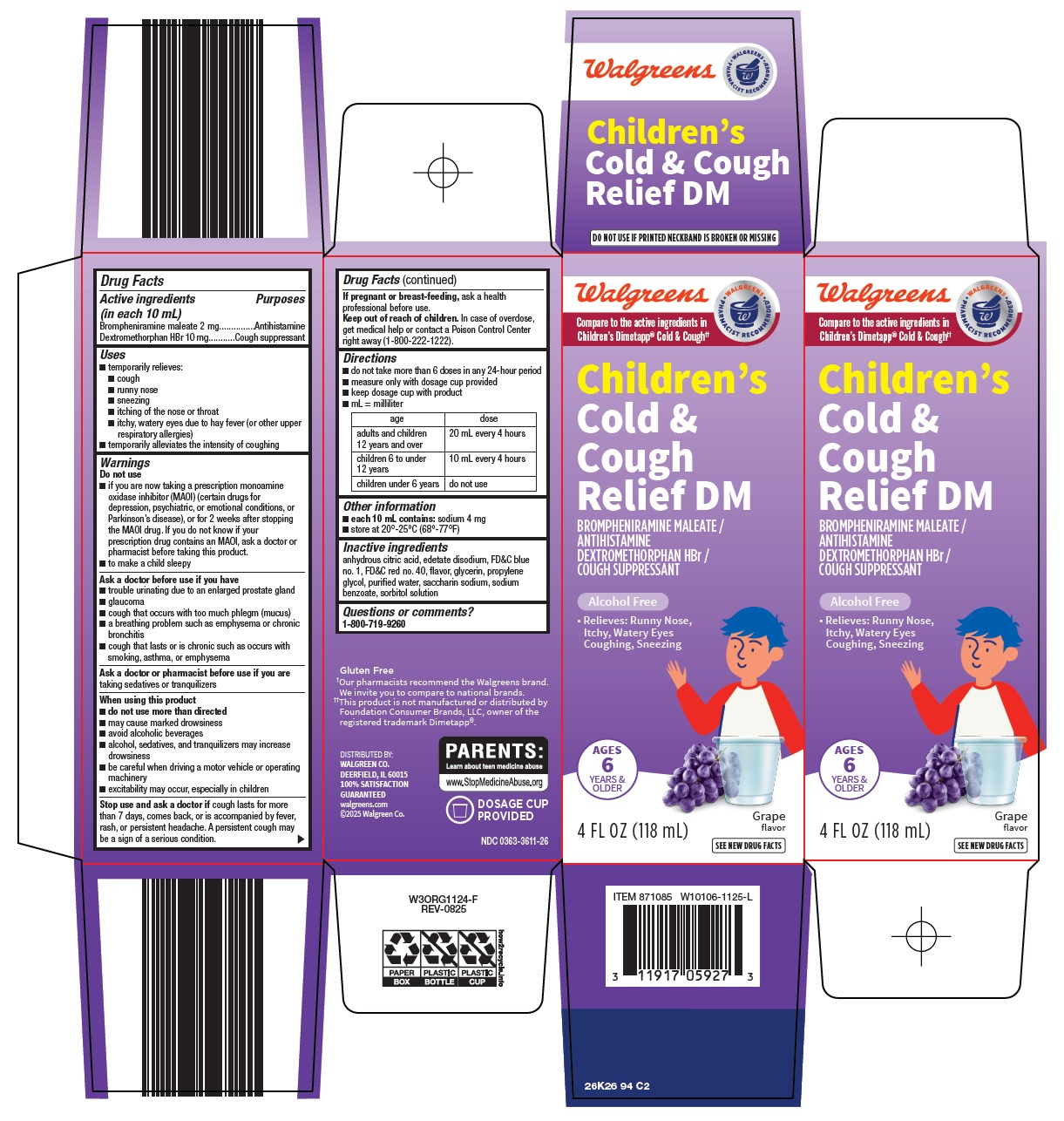 DRUG LABEL: childrens cold and cough relief dm
NDC: 0363-3611 | Form: SOLUTION
Manufacturer: Walgreen Company
Category: otc | Type: HUMAN OTC DRUG LABEL
Date: 20260228

ACTIVE INGREDIENTS: BROMPHENIRAMINE MALEATE 2 mg/10 mL; DEXTROMETHORPHAN HYDROBROMIDE 10 mg/10 mL
INACTIVE INGREDIENTS: ANHYDROUS CITRIC ACID; EDETATE DISODIUM; FD&C BLUE NO. 1; FD&C RED NO. 40; GLYCERIN; PROPYLENE GLYCOL; WATER; SACCHARIN SODIUM; SODIUM BENZOATE; SORBITOL SOLUTION

Walgreen Co. Children’s Cold & Cough Relief DM Drug Facts

Active ingredients (in each 10 mL)

Brompheniramine maleate 2 mg

Dextromethorphan HBr 10 mg

Purposes

Antihistamine

Cough suppressant

Uses

- temporarily relieves:
- cough
- runny nose
- sneezing
- itching of the nose or throat
- itchy, watery eyes due to hay fever (or other upper respiratory allergies)
- temporarily alleviates the intensity of coughing

Warnings

Do not use

- if you are now taking a prescription monoamine oxidase inhibitor (MAOI) (certain drugs for depression, psychiatric, or emotional conditions, or Parkinson’s disease), or for 2 weeks after stopping the MAOI drug. If you do not know if your prescription drug contains an MAOI, ask a doctor or pharmacist before taking this product.
- to make a child sleepy

Ask a doctor before use if you have

- trouble urinating due to an enlarged prostate gland
- glaucoma
- cough that occurs with too much phlegm (mucus)
- a breathing problem such as emphysema or chronic bronchitis
- cough that lasts or is chronic such as occurs with smoking, asthma, or emphysema

Ask a doctor or pharmacist before use if you are

taking sedatives or tranquilizers

When using this product

- do not use more than directed
- may cause marked drowsiness
- avoid alcoholic beverages
- alcohol, sedatives, and tranquilizers may increase drowsiness
- be careful when driving a motor vehicle or operating machinery
- excitability may occur, especially in children

Stop use and ask a doctor if

cough lasts for more than 7 days, comes back, or is accompanied by fever, rash, or persistent headache. A persistent cough may be a sign of a serious condition.

If pregnant or breast-feeding,

ask a health professional before use.

Keep out of reach of children.

In case of overdose, get medical help or contact a Poison Control Center right away (1-800-222-1222).

Directions

- do not take more than 6 doses in any 24-hour period
- measure only with dosage cup provided
- keep dosage cup with product
- mL = milliliter

age | dose
adults and children 12 years over | 20 mL every 4 hours
children 6 to under 12 years | 10 mL every 4 hours
children under 6 years | do not use

Other information

- each 10 mL contains: sodium 4 mg
- store at 20°-25°C (68°-77°F)

Inactive ingredients

anhydrous citric acid, edetate disodium, FD&C blue no. 1, FD&C red no. 40, flavor, glycerin, propylene glycol, purified water, saccharin sodium, sodium benzoate, sorbitol solution

Questions or comments?

1-800-719-9260

Package/Label Principal Display Panel

Walgreens

WALGREENS PHARMACIST RECOMMENDED

Compare to the active ingredients in Children’s Dimetapp® Cold & Cough

Children’s Cold & Cough Relief DM

BROMPHENIRAMINE MALEATE / ANTIHISTAMINE

DEXTROMETHORPHAN HBr / COUGH SUPPRESSANT

Alcohol Free

• Relieves: Runny Nose, Itchy, Watery Eyes

Coughing, Sneezing

AGES 6 YEARS & OLDER

Grape flavor

4 FL OZ (118 mL)

SEE NEW DRUG FACTS